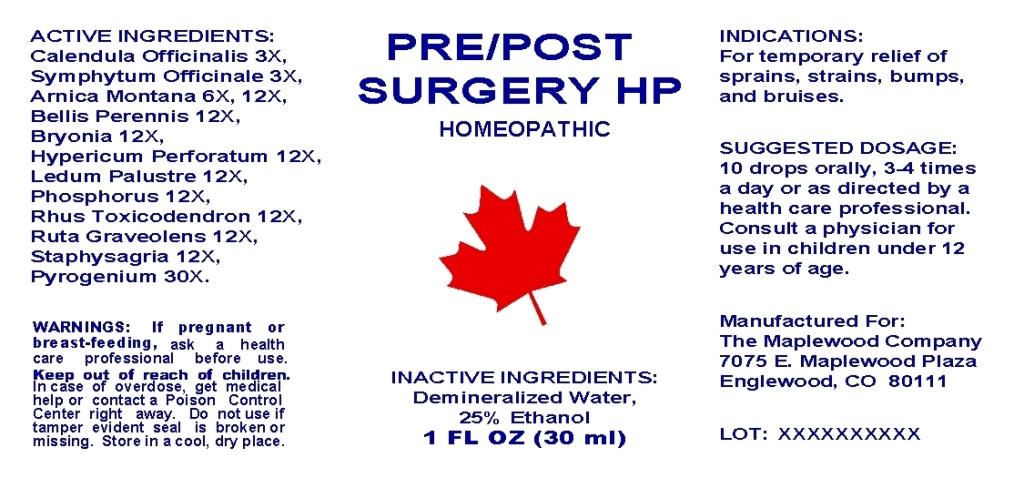 DRUG LABEL: Pre Post Surgery
NDC: 57520-0156 | Form: LIQUID
Manufacturer: Apotheca Company
Category: homeopathic | Type: HUMAN OTC DRUG LABEL
Date: 20101001

ACTIVE INGREDIENTS: ARNICA MONTANA 12 [hp_X]/1 mL; BELLIS PERENNIS 12 [hp_X]/1 mL; BRYONIA ALBA ROOT 12 [hp_X]/1 mL; CALENDULA OFFICINALIS FLOWERING TOP 3 [hp_X]/1 mL; HYPERICUM PERFORATUM 12 [hp_X]/1 mL; LEDUM PALUSTRE TWIG 12 [hp_X]/1 mL; PHOSPHORUS 12 [hp_X]/1 mL; RANCID BEEF 30 [hp_X]/1 mL; TOXICODENDRON PUBESCENS LEAF 12 [hp_X]/1 mL; RUTA GRAVEOLENS FLOWERING TOP 12 [hp_X]/1 mL; DELPHINIUM STAPHISAGRIA SEED 12 [hp_X]/1 mL; COMFREY ROOT 3 [hp_X]/1 mL
INACTIVE INGREDIENTS: WATER; ALCOHOL

Pre/Post Surgery HP

ACTIVE INGREDIENT

ACTIVE INGREDIENTS: Arnica montana 6X, 12X, Bellis perennis 12X, Bryonia 12X, Calendula officinalis 3X, Hypericum perforatum 12X, Ledum palustre 12X, Phosphorus 12X, Pyrogenium 30X, Rhus toxicodendron 12X, Ruta graveolens 12X, Staphysagria 12X, Symphytum officinale 3X.

PURPOSE

INDICATIONS: For temporary relief of sprains, strains, bumps and bruises.

WARNINGS

WARNINGS: If pregnant or breast-feeding, ask a health care professional before use.

Keep out of reach of children. In case of overdose, get medical help or contact a Poison Control Center right away.

Do not use if tamper evident seal is broken or missing. Store in a cool, dry place.

DOSAGE AND ADMINISTRATION

SUGGESTED DOSAGE: 10 drops orally, 3-4 times a day or as directed by a health care professional. Consult a physician for use in children under 12 years of age.

INACTIVE INGREDIENTS: Demineralized water, 25% Ethanol.

KEEP OUT OF REACH OF CHILDREN. In case of overdose, get medical help or contact a Poison Control Center right away.

INDICATIONS AND USAGE

INDICATIONS: For temporary relief of sprains, strains, bumps, and bruises.

QUESTIONS

Manufactured For:

The Maplewood Company

7075 E. Maplewood Plaza

Englewood, CO 80111

PACKAGE LABEL

PRE/POST SURGERY HP

HOMEOPATHIC

1 FL OZ (30 ml)